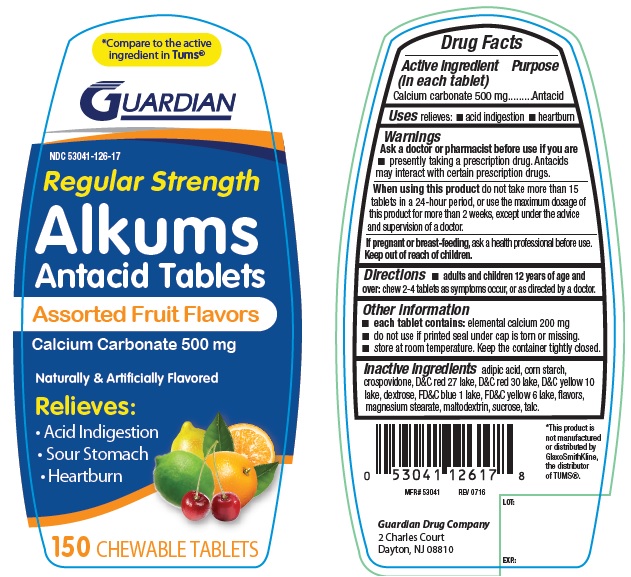 DRUG LABEL: Alkums antacid
NDC: 53041-126 | Form: TABLET, CHEWABLE
Manufacturer: Guardian Drug Company
Category: otc | Type: HUMAN OTC DRUG LABEL
Date: 20250206

ACTIVE INGREDIENTS: CALCIUM CARBONATE 500 mg/1 1
INACTIVE INGREDIENTS: ADIPIC ACID; STARCH, CORN; CROSPOVIDONE; D&C RED NO. 27; D&C RED NO. 30; D&C YELLOW NO. 10; DEXTROSE; FD&C BLUE NO. 1; FD&C YELLOW NO. 6; MAGNESIUM STEARATE; MALTODEXTRIN; SUCROSE; TALC

Alkums Regular strength Antacid Assorted Fruit Tablets

Active ingredient (in each tablet)

Calcium carbonate 500 mg

Purpose

Antacid

Uses

relieves

- acid indigestion
- heartburn

Warnings

Ask a doctor or pharmacist before use if you are

taking a prescription drug. Antacids may interact with certain prescriptiom drugs.

When using this product

do not take more than 16 tablets in a 24-hour period, or use the maximum dosage of this product for more than 2 weeks, except under the advice and supervision of a doctor.

Directions

- chew 2-4 tablets as symptoms occur, or as directed by a doctor

Other information

- do not use if printed seal under cap is torn or missing
- store at room temperature

Inactive ingredients

adipic acid, corn starch, crospovidone, D&C red 27 lake, D&C red 30 lake, D&C Yellow 10 lake, dextrose, FD&C blue 1 lake, FD&C yellow 6 lake, flavors, magnesium stearate, maltodextrin, sucrose, talc

Principal Display Panel

*compare to the active ingredient in Tums®

NDC 53041-126-17

Regular Strength

Alkums antacid tablets

Assorted fruit flavors

calcium carbonate 500 mg

Relieves:

heartburn

acid indigestion

sour stomach

150 chewable tablets